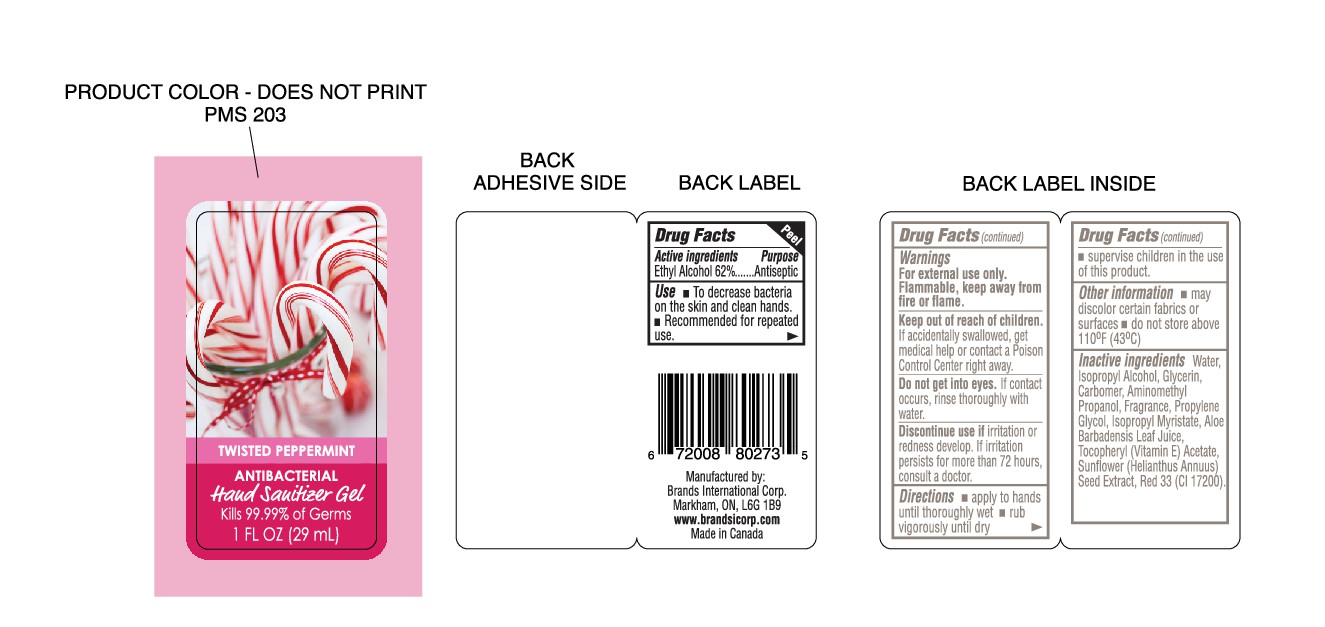 DRUG LABEL: TWISTED PEPPERMINT
NDC: 50157-110 | Form: GEL
Manufacturer: Brands International
Category: otc | Type: HUMAN OTC DRUG LABEL
Date: 20161004

ACTIVE INGREDIENTS: ALCOHOL 620 mL/1000 mL
INACTIVE INGREDIENTS: WATER; ISOPROPYL ALCOHOL; GLYCERIN; CARBOMER HOMOPOLYMER TYPE C (ALLYL PENTAERYTHRITOL CROSSLINKED); AMINOMETHYLPROPANOL; PROPYLENE GLYCOL; ISOPROPYL MYRISTATE; ALOE VERA LEAF; .ALPHA.-TOCOPHEROL ACETATE; HELIANTHUS ANNUUS SEED WAX; FD&C RED NO. 40; FD&C YELLOW NO. 5; FD&C BLUE NO. 1

TWISTED PEPPERMINT ANTIBACTERIAL HAND SANITIZER

ACTIVE INGREDIENT: ETHYL ALCOHOL 62% PURPOSE ANTISEPTIC

PURPOSE

ANTISEPTIC

INDICATIONS AND USAGE

USES: TO DECREASE BACTERIA ON THE SKIN AND CLEAN HANDS. RECOMMENDED FOR REPEATED USE

WARNINGS

WARNING: FOR EXTERNAL USE ONLY. FLAMMABLE, KEEP AWAY FROM FIRE OR FLAME.

WHEN USING

DO NOT GET INTO EYES. IF CONTACT OCCURS,RINSE THROUGHLY WITH WATER.

ASK DOCTOR

DISCONTINUE USE IF IRRITATION OR REDNESS DEVELOP. IF IRRITATION PERSISTS FOR MORE THEN 72 HOURS, CONSULT A DOCTOR.

SUPERVISE CHILDREN IN THE USE OF THIS PRODUCT.

DOSAGE AND ADMINISTRATION

OTHER INFORMATIONMAY DISCOLOR CERTAIN FEBRICS OR SURFACES.

INACTIVE INGREDIENT

INACTIVE INGREDIENTS: WATER, PISOPROPYL ALCOHOL, GLYCERIN, CARBOMER, AMINOMETHYL PROPANOL, PROPYLENE GLYCOL, ISOPROPYL MYRISTATE, ALOE BARBADENSIS LEAF JUICE, TOCOPHEROL ACETATE, SUNFLOWER (HELIANTHUS ANNUUS) SEED EXTRACT, MAY CONTAIN: FD&C BLUE NO. 1(CI 42090), FD&C RED NO. 40(CI 16035), FD&C YELLOW NO. 5 (CI 19140)